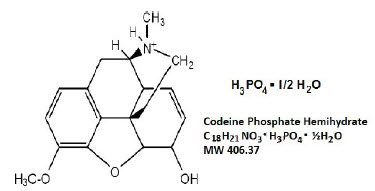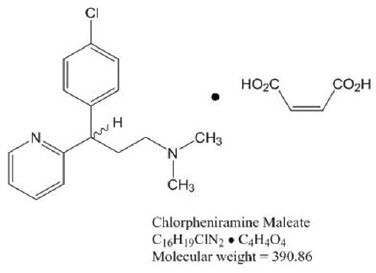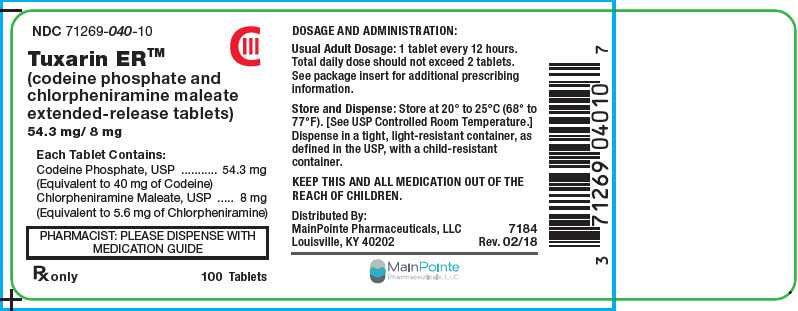 DRUG LABEL: Tuxarin
NDC: 71269-040 | Form: TABLET, EXTENDED RELEASE
Manufacturer: Mainpointe Pharmaceuticals
Category: prescription | Type: HUMAN PRESCRIPTION DRUG LABEL
Date: 20240110
DEA Schedule: CIII

ACTIVE INGREDIENTS: CODEINE PHOSPHATE 54.3 mg/1 1; CHLORPHENIRAMINE MALEATE 8 mg/1 1

HIGHLIGHTS OF PRESCRIBING INFORMATION

These highlights do not include all the information needed to use TUXARIN ER™ safely and effectively. See full prescribing information for TUXARIN ER.
TUXARIN ER (codeine phosphate and chlorpheniramine maleate) extended-release tablets, for oral use, CIII
Initial U.S. Approval: 1985

WARNING: ADDICTION, ABUSE, AND MISUSE; LIFE-THREATENING RESPIRATORY DEPRESSION; ACCIDENTIAL INGESTION; ULTRA-RAPID METABOLISM OF CODEINE AND OTHER RISK FACTORS FOR LIFE-THREATENING RESPIRATORY DEPRESSION IN CHILDREN; MEDICATION ERRORS; INTERACTIONS WITH DRUGS AFFECTING CYTOCHROME P450 ISOENZYMES; CONCOMITANT USE WITH BENZODIAZEPINES OR OTHER CNS DEPRESSANTS; NEONATAL OPOID WITHDRAWAL SYNDROME

See full prescribing information for complete boxed warning.

- TUXARIN ER exposes users to risks of addiction, abuse, and misuse, which can lead to overdose and death. Assess patient's risk before prescribing and monitor closely for these behaviors and conditions. (5.1)
- Serious, life-threatening, or fatal respiratory depression may occur. Monitor closely, especially upon initiation or when used in patients at higher risk. (5.2)
- Accidental ingestion of TUXARIN ER, especially by children, can result in a fatal overdose of codeine. (5.2)
- Life-threatening respiratory depression and death have occurred in children who received codeine; most cases followed tonsillectomy and/or adenoidectomy, and many of the children had evidence of being an ultra-rapid metabolizer of codeine due to a CYP2D6 polymorphism. (5.3) TUXARIN ER is contraindicated in children younger than 12 years of age and in children younger than 18 years of age following tonsillectomy and/or adenoidectomy. (4) Avoid the use of TUXARIN ER in adolescents 12 to 18 years of age who have other risk factors that may increase their sensitivity to the respiratory depressant effects of codeine.
- Ensure accuracy when prescribing, dispensing, and administering TUXARIN ER. Dosing errors can result in accidental overdose and death. (2.1, 5.6)
- The effects of concomitant use or discontinuation of cytochrome P450 3A4 inducers, 3A4 inhibitors, or 2D6 inhibitors with codeine are complex, requiring careful consideration of the effects on the parent drug, codeine, and the active metabolite, morphine. Avoid the use of TUXARIN ER in these patients. (5.4, 7.1, 7.2, 7.4)
- Concomitant use of opioids with benzodiazepines or other central nervous system (CNS) depressants, including alcohol, may result in profound sedation, respiratory depression, coma, and death. Avoid the use of TUXARIN ER in patients taking benzodiazepines, other CNS depressants, or alcohol. (5.9, 7.5)
- TUXARIN ER is not recommended for use in pregnant women. Prolonged use of TUXARIN ER during pregnancy can result in neonatal opioid withdrawal syndrome, which may be life-threatening if not recognized and treated. If TUXARIN ER is used for a prolonged period in a pregnant woman, advise the patient of the risk of neonatal opioid withdrawal syndrome and ensure that appropriate treatment will be available. (5.15, 8.1)

1 INDICATIONS AND USAGE

TUXARIN ER is a combination of codeine, an opioid agonist; and chlorpheniramine, a histamine-1 (H1) receptor antagonist, indicated for the temporary relief of cough and upper respiratory symptoms associated with allergy or the common cold in patients 18 years of age and older. (1)

Important Limitations of Use (1)

- Not indicated for pediatric patients under 18 years of age.
- Because of the risks of addiction, abuse, and misuse with opioids, even at recommended doses, reserve TUXARIN ER for use in adult patients for whom the benefits of cough suppression are expected to outweigh the risks, and in whom an adequate assessment of the etiology of the cough has been made.

2 DOSAGE AND ADMINISTRATION

- Adults 18 years of age and older: 1 tablet every 12 hours as needed, not to exceed 2 tablets in 24 hours. (2.2)
- Do not increase the dose or dosing frequency. (2.1)
- Prescribe for the shortest duration consistent with treatment goals. (2.3)
- Reevaluate patients with unresponsive cough in 5 days or sooner for possible underlying pathology. (2.3)
- Reevaluate patient prior to refilling. (2.3)

3 DOSAGE FORMS AND STRENGTHS

Extended-release (ER) tablet: contains 54.3 mg of codeine phosphate; and 8 mg of chlorpheniramine maleate. (3)

4 CONTRAINDICATIONS

- Children younger than 12 years of age (4)
- Significant respiratory depression. (4)
- Acute or severe bronchial asthma in an unmonitored setting or in absence of resuscitative equipment. (4)
- Known or suspected gastrointestinal obstruction, including paralytic ileus. (4)
- Concurrent use of monoamine oxidase inhibitor (MAOI) therapy or within the last 14 days. (4)
- Hypersensitivity to codeine or other opiates, chlorpheniramine, or any of the inactive ingredients in TUXARIN ER. (4)

5 WARNINGS AND PRECAUTIONS

See Boxed WARNINGS

- Life-threatening respiratory depression in patients with chronic pulmonary disease or in elderly, cachectic, or debilitated patients: Monitor closely, particularly during initiation of therapy. (5.5)
- Activities requiring mental alertness: Avoid engaging in hazardous tasks requiring mental alertness such as driving or operating machinery. (5.7)
- Risks of use in patients with head injury, impaired consciousness, increased intracranial pressure, or brain tumors: Avoid use. May increase intracranial pressure and obscure the clinical course of head injuries. (5.11)
- Seizures in patients with seizure disorders: Monitor during therapy. (5.12)
- Severe hypotension: Monitor during initiation of therapy. Avoid use in patients with circulatory shock. (5.14)
- Adrenal insufficiency: If diagnosed, treat with physiologic replacement of corticosteroids, and wean patient off of the opioid. (5.16)

6 ADVERSE REACTIONS

Common adverse reactions of TUXARIN ER include: Sedation (somnolence, mental clouding, lethargy), impaired mental and physical performance, lightheadedness, dizziness, headache, dry mouth, nausea, vomiting, constipation, shortness of breath, and sweating. (6)

To report SUSPECTED ADVERSE REACTIONS, contact MainPointe Pharmaceuticals, LLC at 502-709-7544 or go to mainpointepharmaceuticals.com or FDA at 1-800-FDA-1088 or www.fda.gov/medwatch.

7 DRUG INTERACTIONS

- Phenytoin: Avoid concomitant use; may increase phenytoin levels. (7.4)
- Serotonergic drugs: Concomitant use may result in serotonin syndrome. Discontinue if serotonin syndrome is suspected. (7.6)
- Muscle relaxants: Avoid concomitant use. (7.8)
- Diuretics: Codeine may reduce the efficacy of diuretics. Monitor for reduced effect. (7.9)
- Anticholinergic drugs: Concurrent use may cause paralytic ileus. (5.10, 7.10)

8 USE IN SPECIFIC POPULATIONS

- Pregnancy: Avoid use in pregnant women. May cause fetal harm. (8.1)
- Lactation: Breastfeeding not recommended. (8.2)
- Renal Impairment: Use with caution in patients with severe renal impairment. (8.6)
- Hepatic Impairment: Use with caution in patients with severe hepatic impairment. (8.7)

FULL PRESCRIBING INFORMATION

WARNING: ADDICTION, ABUSE, AND MISUSE; LIFE-THREATENING RESPIRATORY DEPRESSION; ACCIDENTIAL INGESTION; ULTRA-RAPID METABOLISM OF CODEINE AND OTHER RISK FACTORS FOR LIFE-THREATENING RESPIRATORY DEPRESSION IN CHILDREN; MEDICATION ERRORS; INTERACTIONS WITH DRUGS AFFECTING CYTOCHROME P450 ISOENZYMES; CONCOMITANT USE WITH BENZODIAZEPINES OR OTHER CNS DEPRESSANTS; NEONATAL OPOID WITHDRAWAL SYNDROME

Addiction, Abuse, and Misuse

TUXARIN ER exposes patients and other users to the risks of opioid addiction, abuse, and misuse, which can lead to overdose and death. Reserve TUXARIN ER for use in adult patients for whom the benefits of cough suppression are expected to outweigh the risks, and in whom an adequate assessment of the etiology of the cough has been made. Assess each patient's risk prior to prescribing TUXARIN ER, prescribe TUXARIN ER for the shortest duration that is consistent with individual patient treatment goals, monitor all patients regularly for the development of addition or abuse, and refill only after reevaluation of the need for continued treatment. [see Warnings and Precautions (5.1)]

Life-Threatening Respiratory Depression

Serious, life-threatening, or fatal respiratory depression may occur with use of TUXARIN ER. Monitor for respiratory depression, especially during initiation of TUXARIN ER therapy or when used in patients at higher risk [see Warnings and Precautions (5.2)].

Accidental Ingestion

Accidental ingestion of even one dose of TUXARIN ER, especially by children, can result in a fatal overdose of codeine [see Warnings and Precautions (5.2)].

Ultra-Rapid Metabolism of Codeine and Other Risk Factors for Life-Threatening Respiratory Depression in Children

Life threatening respiratory depression and death have occurred in children who received codeine. Most of the reported cases occurred following tonsillectomy and/or adenoidectomy, and many of the children had evidence of being an ultra-rapid metabolizer of codeine due to a CYP2D6 polymorphism. [See Warnings and Precautions (5.3)]. TUXARIN ER is contraindicated in children younger than 12 years of age and in children younger than 18 years of age following tonsillectomy and/or adenoidectomy [See Contraindications (4)]. Avoid the use of TUXARIN ER in adolescents 12 to 18 years of age who have other risk factors that may increase their sensitivity to the respiratory depressant effects of codeine. [See Warnings and Precautions (5.1)].

Risk of Medication Errors

Ensure accuracy when prescribing, dispensing, and administering TUXARIN ER. Dosing errors can result in accidental overdose and death. [see Dosage and Administration (2.1), Warnings and Precautions (5.6)].

Interactions with Drugs Affecting Cytochrome P450 Isoenzymes

The effects of concomitant use or discontinuation of cytochrome P450 3A4 inducers, 3A4 inhibitors, or 2D6 inhibitors with codeine are complex, requiring careful consideration of the effects on the parent drug, codeine, and the active metabolite, morphine. Avoid the use of TUXARIN ER in patients who are taking a CYP3A4 inhibitor, CYP3A4 inducer, or 2D6 inhibitor [see Warnings and Precautions (5.8), Drug Interactions (7.1, 7.2, 7.4)].

Risks from Concomitant Use with Benzodiazepines, CNS Depressants

Concomitant use of opioids with benzodiazepines or other central nervous system (CNS) depressants, including alcohol, may result in profound sedation, respiratory depression, coma, and death. Avoid use of TUXARIN ER in patients taking benzodiazepines, other CNS depressants, or alcohol. [see Warning and Precautions (5.9) Drug Interactions (7.5)].

Neonatal Opioid Withdrawal Syndrome

TUXARIN ER is not recommended for use in pregnant women [see Use in Specific Populations (8.1)]. Prolonged use of TUXARIN ER during pregnancy can result in neonatal opioid withdrawal syndrome, which may be life-threatening if not recognized and treated, and requires management according to protocols developed by neonatology experts. If TUXARIN ER is used for a prolonged period in a pregnant woman, advise the patient of the risk of neonatal opioid withdrawal syndrome and ensure that appropriate treatment will be available [see Warnings and Precautions (5.15)].

1 INDICATIONS AND USAGE

TUXARIN ER is indicated for the temporary relief of cough and upper respiratory symptoms associated with allergy or the common cold in patients 18 years of age and older.

Important Limitations of Use

- Not indicated for pediatric patients under 18 years of age [see Use in Specific Population (8.4)].
- Contraindicated in pediatric patients under 12 years of age [see Contraindications (4), Use in Specific Populations (8.4)].
- Contraindicated in pediatric patients 12 to 18 years of age after tonsillectomy or adenoidectomy [see Contraindications (4), Use in Specific Populations (8.4)].
- Because of the risks of addiction, abuse, and misuse with opioids, even at recommended doses [see Warnings and Precautions (5.1)], reserve TUXARIN ER for use in adult patients for whom the benefits of cough suppression are expected to outweigh the risks, and in whom an adequate assessment of the etiology of the cough has been made.

2 DOSAGE AND ADMINISTRATION

2.1 Important Dosage and Administration Instructions

Administer TUXARIN ER by the oral route only.

Advise patients not to increase the dose or dosing frequency of TUXARIN ER because serious adverse events such as respiratory depression may occur with overdosage [see Warnings and Precautions (5.2), Overdosage (10)]. The dosage of TUXARIN ER should not be increased if cough fails to respond; an unresponsive cough should be reevaluated for possible underlying pathology [see Dosage and Administration (2.3), Warnings and Precautions (5.5)].

2.2 Recommended Dosage

Adults 18 years of age and older: one tablet every 12 hours as needed, not to exceed 2 tablets in 24 hours.

2.3 Monitoring, Maintenance, and Discontinuation of Therapy

Prescribe TUXARIN ER for the shortest duration that is consistent with individual patient treatment goals [see Warnings and Precautions (5.1)]

Monitor patients closely for respiratory depression, especially within the first 24-72 hours of initiating therapy [see Warnings and Precautions (5.2)].

Reevaluate patients with unresponsive cough in 5 days or sooner for possible underlying pathology, such as foreign body or lower respiratory tract disease [see Warnings and Precautions (5.5)]. If a patient requires a refill, reevaluate the cause of the cough and assess the need for continued treatment with TUXARIN ER, the relative incidence of adverse reactions, and the development of addiction, abuse, or misuse [see Warnings and Precautions (5.1)].

Do not abruptly discontinue TUXARIN ER in a physically-dependent patient [see Drug Abuse and Dependence (9.3)]. When a patient who has been taking TUXARIN ER regularly and may be physically dependent no longer requires therapy with TUXARIN ER, taper the dose gradually, by 25% to 50% every 2 to 4 days, while monitoring carefully for signs and symptoms of withdrawal. If the patient develops these signs or symptoms, raise the dose to the previous level and taper more slowly, either by increasing the interval between decreases, decreasing the amount of change in dose, or both.

3 DOSAGE FORMS AND STRENGTHS

Extended-release tablets: Each tablet contains 54.3 mg of codeine phosphate (equivalent to 40 mg of codeine); and 8 mg of chlorpheniramine maleate (equivalent to 5.6 mg of chlorpheniramine). Each tablet is white to off-white, uncoated, round, debossed with MP on one side and CC on the other side [see Description (11)].

4 CONTRAINDICATIONS

TUXARIN ER is contraindicated for:

- All children younger than 12 years of age [see Warnings and Precautions (5.2, 5.3, 5.4), Use in Specific Populations (8.4)].
- Postoperative management in children younger than 18 years of age following tonsillectomy and/or adenoidectomy [see Warnings and Precautions (5.2, 5.3)].

TUXARIN ER is also contraindicated in patients with:

- Significant respiratory depression [see Warnings and Precautions (5.2)]
- Acute or severe bronchial asthma in an unmonitored setting or in the absence of resuscitative equipment [see Warnings and Precautions (5.5)].
- Known or suspected gastrointestinal obstruction, including paralytic ileus [see Warnings and Precautions (5.10)].
- Concurrent use of monoamine oxidase inhibitors (MAOIs) or use of MAOIs within 14 days [see Warnings and Precautions (5.13), Drug Interactions (7.7)].
- Hypersensitivity to codeine, chlorpheniramine, or any of the inactive ingredients in TUXARIN ER [see Adverse Reactions (6)]. Persons known to be hypersensitive to certain other opioids may exhibit cross-reactivity to codeine.

5 WARNINGS AND PRECAUTIONS

5.1 Addiction, Abuse, and Misuse

TUXARIN ER contains codeine, a Schedule III controlled substance. As an opioid, TUXARIN ER exposes users to the risks of addiction, abuse, and misuse [see Drug Abuse and Dependence (9)], which can lead to overdose and death [see Overdosage (10)]. Reserve TUXARIN ER for use in adult patients for whom the benefits of cough suppression are expected to outweigh the risks, and in whom an adequate assessment of the etiology of the cough has been made. Assess each patient's risk prior to prescribing TUXARIN ER, prescribe TUXARIN ER for the shortest duration that is consistent with individual patient treatment goals, monitor all patients regularly for the development of addiction or abuse, and refill only after reevaluation of the need for continued treatment.

Although the risk of addiction in any individual is unknown, it can occur in patients appropriately prescribed TUXARIN ER. Addiction can occur at recommended dosages and if the drug is misused or abused. Risks are increased in patients with a personal or family history of substance abuse (including drug or alcohol abuse or addiction) or mental illness (e.g., major depression).

Opioids are sought by drug abusers and people with addiction disorders and are subject to criminal diversion. Consider these risks when prescribing or dispensing TUXARIN ER. Strategies to reduce these risks include prescribing the drug in the smallest appropriate quantity and advising the patient on the proper disposal of unused drug [see Patient Counseling Information (17)]. Contact local state professional licensing board or state controlled substances authority for information on how to prevent and detect abuse or diversion of this product.

5.2 Life-Threatening Respiratory Depression

Serious, life-threatening, or fatal respiratory depression has been reported with the use of opioids, including codeine, one of the active ingredients in TUXARIN ER. Codeine produces dose-related respiratory depression by directly acting on the brain stem respiratory center that controls respiratory rhythm and may produce irregular and periodic breathing. Codeine is subject to variability in metabolism based upon CYP2D6 genotype, which can lead to an increased exposure to the active metabolite morphine [see Warnings and Precautions (5.3)]. Respiratory depression, if not immediately recognized and treated, may lead to respiratory arrest and death. Management of respiratory depression includes discontinuation of TUXARIN ER, close observation, supportive measures, and use of opioid antagonists (e.g. naloxone), depending on the patient's clinical status [see Overdosage (10)]. Carbon dioxide (CO2) retention from opioid-induced respiratory depression can exacerbate the sedating effects of opioids.

While serious, life-threatening, or fatal respiratory depression can occur at any time during the use of TUXARIN ER, the risk is greatest during the initiation of therapy, when TUXARIN ER is used concomitantly with other drugs that may cause respiratory depression [see Warnings and Precautions (5.9)], in patients with chronic pulmonary disease or decreased respiratory reserve, and in patients with altered pharmacokinetics or altered clearance (e.g. elderly, cachectic, or debilitated patients) [see Warnings and Precautions (5.5)].

To reduce the risk of respiratory depression, proper dosing of TUXARIN ER is essential [see Dosage and Administration (2.1), Warnings and Precautions (5.6)]. Monitor patients closely, especially within the first 24- 72 hours of initiating therapy or when used in patients at higher risk.

Overdose of codeine in adults has been associated with fatal respiratory depression, and the use of codeine in children younger than 12 years of age has been associated with fatal respiratory depression when used as recommended [see Warnings and Precautions (5.3)]. Accidental ingestion of even one dose of TUXARIN ER, especially by children, can result in respiratory depression and death.

5.3 Ultra-Rapid Metabolism of Codeine and Other Risk Factors for Life-Threatening Respiratory Depression in Children

Life-threatening respiratory depression and death have occurred in children who received codeine. Codeine is subject to variability in metabolism based upon CYP2D6 genotype (described below), which can lead to an increased exposure to the active metabolite morphine. Based upon post-marketing reports, children younger than 12 years old appear to be more susceptible to the respiratory depressant effects of codeine, particularly if there are risk factors for respiratory depression. For example, many reported cases of death occurred in the post-operative period following tonsillectomy and/or adenoidectomy, and many of the children had evidence of being ultra-rapid metabolizers of codeine. Furthermore, children with obstructive sleep apnea who are treated with codeine for post-tonsillectomy and/or adenoidectomy pain may be particularly sensitive to its respiratory depressant effect. Because of the risk of life-threatening respiratory depression and death:

- TUXARIN ER is contraindicated in all children younger than 12 years of age [see Contraindications (4)].
- TUXARIN ER is contraindicated for post-operative management in pediatric patients younger than 18 years of age following tonsillectomy and/or adenoidectomy [see Contraindications (4)].
- Avoid the use of TUXARIN ER in adolescents 12 to 18 years of age who have other risk factors that may increase their sensitivity to the respiratory depressant effects of codeine. Risk factors include conditions associated with hypoventilation, such as postoperative status, obstructive sleep apnea, obesity, severe pulmonary disease, neuromuscular disease, and concomitant use of other medications that cause respiratory depression. [see Warnings and Precautions (5.9), Use in Specific Populations (8.4)]
- Healthcare providers should choose the lowest effective dose for the shortest period of time and inform patients and caregivers about these risks and the signs of morphine overdose [see Warnings and Precautions (5.1), Overdosage (10)].

Lactation

At least one death was reported in a nursing infant who was exposed to high levels of morphine in breast milk because the mother was an ultra-rapid metabolizer of codeine. Breastfeeding is not recommended during treatment with TUXARIN ER [see Use in Specific Populations (8.2)].

CYP2D6 Genetic Variability: Ultra-Rapid Metabolizers

Some individuals may be ultra-rapid metabolizers because of a specific CYP2D6 genotype (e.g., gene duplications denoted as *1/*1×N or *1/*2×N). The prevalence of this CYP2D6 phenotype varies widely and has been estimated at 1 to 10% for Whites (European, North American), 3 to 4% for Blacks (African Americans), 1 to 2% for East Asians (Chinese, Japanese, Korean), and may be greater than 10% in certain /ethnic groups (i.e., Oceanian, Northern African, Middle Eastern, Ashkenazi Jews, Puerto Rican). These individuals convert codeine into its active metabolite, morphine, more rapidly and completely than other people. This rapid conversion results in higher than expected serum morphine levels. Even at labeled dosage regimens, individuals who are ultra-rapid metabolizers may have life-threatening or fatal respiratory depression or experience signs of overdose (such as extreme sleepiness, confusion, or shallow breathing) [see Overdosage (10)]. Therefore, individuals who are ultra-rapid metabolizers should not use TUXARIN ER.

5.4 Risks with Use in Pediatric Populations

Children are particularly sensitive to the respiratory depressant effects of codeine [see Warnings and Precautions (5.2, 5.3)]. Because of the risk of life-threatening respiratory depression and death, TUXARIN ER is contraindicated in children less than 12 years of age, and in pediatric patients younger than 18 years of age following tonsillectomy and/or adenoidectomy [see Contraindications (4)].

Use of TUXARIN ER in children also exposes them to the risks of addiction, abuse, and misuse [see Drug Abuse and Dependence (9)], which can lead to overdose and death [see Warnings and Precautions (5.1), Overdosage (10)]. Because the benefits of symptomatic treatment of cough associated with allergies or the common cold do not outweigh the risks of use of codeine in pediatric patients, TUXARIN ER is not indicated for use in patients younger than 18 years of age [see Indications (1), Use in Specific Populations (8.4)].

5.5 Risks with Use in Other At-Risk Populations

Unresponsive Cough

The dosage of TUXARIN ER should not be increased if cough fails to respond; an unresponsive cough should be reevaluated in 5 days or sooner for possible underlying pathology, such as foreign body or lower respiratory tract disease [see Dosage and Administration (2.3)].

Asthma and Other Pulmonary Disease

The use of TUXARIN ER in patients with acute or severe bronchial asthma in an unmonitored setting or in the absence of resuscitative equipment is contraindicated [see Contraindications (4)].

Opioid analgesics and antitussives, including codeine, one of the active ingredients in TUXARIN ER, should not be used in patients with acute febrile illness associated with productive cough or in patients with chronic respiratory disease where interference with ability to clear the tracheobronchial tree of secretions would have a deleterious effect on the patient's respiratory function.

TUXARIN ER-treated patients with significant chronic obstructive pulmonary disease or cor pulmonale, and those with a substantially decreased respiratory reserve, hypoxia, hypercapnia, or pre-existing respiratory depression are at increased risk of decreased respiratory drive including apnea, even at recommended dosages of TUXARIN ER [see Warnings and Precautions (5.2)].

Elderly, Cachectic, or Debilitated Patients: Life-threatening respiratory depression is more likely to occur in elderly, cachectic, or debilitated patients because they may have altered pharmacokinetics or altered clearance compared to younger, healthier patients [see Warnings and Precautions (5.2)].

Because of the risk of respiratory depression, avoid the use of opioid antitussives, including TUXARIN ER in patients with compromised respiratory function, patients at risk of respiratory failure, and in elderly, cachectic, or debilitated patients. If TUXARIN ER is prescribed, monitor such patients closely, particularly when initiating TUXARIN ER and when TUXARIN ER is given concomitantly with other drugs that depress respiration [see Warnings and Precautions (5.9)].

5.6 Risk of Accidental Overdose and Death due to Medication Errors

Dosing errors can result in accidental overdose and death. To reduce the risk of overdose and respiratory depression, ensure that the dose of TUXARIN ER is communicated clearly and dispensed accurately [see Dosage and Administration (2.1)].

5.7 Activities Requiring Mental Alertness: Risks of Driving and Operating Machinery

Codeine and chlorpheniramine, the active ingredients in TUXARIN ER, may produce marked drowsiness and impair the mental and/or physical abilities required for the performance of potentially hazardous tasks such as driving a car or operating machinery. Advise patients to avoid engaging in hazardous tasks requiring mental alertness and motor coordination after ingestion of TUXARIN ER. Avoid concurrent use of TUXARIN ER with alcohol or other central nervous system depressants because additional impairment of central nervous system performance may occur [See Warnings and Precautions (5.9)].

5.8 Risks of Interactions with Drugs Affecting Cytochrome P450 Isoenzymes

The effects of concomitant use or discontinuation of cytochrome P450 3A4 inducers, 3A4 inhibitors, or 2D6 inhibitors with codeine are complex. Use of cytochrome P450 3A4 inducers, 3A4 inhibitors, or 2D6 inhibitors with TUXARIN ER requires careful consideration of the effects on the parent drug, codeine, and the active metabolite, morphine.

Cytochrome P450 3A4 Interaction

The concomitant use of TUXARIN ER with all cytochrome P450 3A4 inhibitors, such as macrolide antibiotics (e.g., erythromycin), azole-antifungal agents (e.g., ketoconazole), and protease inhibitors (e.g., ritonavir) or discontinuation of a cytochrome P450 3A4 inducer such as rifampin, carbamazepine, and phenytoin, may result in an increase in codeine plasma concentrations with subsequently greater metabolism by cytochrome P450 2D6, resulting in greater morphine levels, which could increase or prolong adverse reactions and may cause potentially fatal respiratory depression.

The concomitant use of TUXARIN ER with all cytochrome P450 3A4 inducers or discontinuation of a cytochrome P450 3A4 inhibitor may result in lower codeine levels, greater norcodeine levels, and less metabolism via 2D6 with resultant lower morphine levels. This may be associated with a decrease in efficacy, and in some patients, may result in signs and symptoms of opioid withdrawal.

Avoid the use of TUXARIN ER in patients who are taking a CYP3A4 inhibitor or CYP3A4 inducer. If concomitant use of TUXARIN ER with inhibitors and inducers of CYP3A4 is necessary, monitor patients for signs and symptoms that may reflect opioid toxicity and opioid withdrawal [see Drug Interactions (7.1, 7.2)].

Risks of Concomitant Use or Discontinuation of Cytochrome P450 2D6 Inhibitors

The concomitant use of TUXARIN ER with all cytochrome P450 2D6 inhibitors (e.g., amiodarone, quinidine) may result in an increase in codeine plasma concentrations and a decrease in active metabolite morphine plasma concentration which could result in an analgesic efficacy reduction or symptoms of opioid withdrawal.

Discontinuation of a concomitantly used cytochrome P450 2D6 inhibitor may result in a decrease in codeine plasma concentration and an increase in active metabolite morphine plasma concentration which could increase or prolong adverse reactions and may cause potentially fatal respiratory depression.

Avoid the use of TUXARIN ER in patients who are taking a CYP2D6 inhibitor. If concomitant use of TUXARIN ER with inhibitors of CYP2D6 is necessary, monitor patients for signs and symptoms that may reflect opioid toxicity and opioid withdrawal [see Drug Interactions (7.4)].

5.9 Risks from Concomitant Use with Benzodiazepines or other CNS Depressants

Concomitant use of opioids, including TUXARIN ER, with benzodiazepines, or other CNS depressants, including alcohol, may result in profound sedation, respiratory depression, coma, and death. Because of these risks, avoid use of opioid cough medications in patients taking benzodiazepines, other CNS depressants, or alcohol [see Drug Interactions (7.5)].

Observational studies have demonstrated that concomitant use of opioid analgesics and benzodiazepines increases the risk of drug-related mortality compared to use of opioids alone. Because of similar pharmacologic properties, it is reasonable to expect similar risk with concomitant use of opioid cough medications and benzodiazepines, other CNS depressants, or alcohol.

Advise both patients and caregivers about the risks of respiratory depression and sedation if TUXARIN ER is used with benzodiazepines, alcohol, or other CNS depressants [see Patient Counseling Information (17)].

5.10 Risks of Use in Patients with Gastrointestinal Conditions

TUXARIN ER is contraindicated in patients with known or suspected gastrointestinal obstruction, including paralytic ileus [see Contraindications (4)]. The use of codeine in TUXARIN ER may obscure the diagnosis or clinical course of patients with acute abdominal conditions.

The concurrent use of anticholinergics with TUXARIN ER may produce paralytic ileus [see Drug Interactions (7.10)].

The codeine in TUXARIN ER may result in constipation or obstructive bowel disease, especially in patients with underlying intestinal motility disorders. Use with caution in patients with underlying intestinal motility disorders.

The codeine in TUXARIN ER may cause spasm of the sphincter of Oddi, resulting in an increase in biliary tract pressure. Opioids may cause increases in serum amylase [see Warnings and Precautions (5.17)]. Monitor patients with biliary tract disease, including acute pancreatitis for worsening symptoms.

5.11 Risks of Use in Patients with Head Injury, Impaired Consciousness, Increased Intracranial Pressure, or Brain Tumors

Avoid the use of TUXARIN ER in patients with head injury, intracranial lesions, or a pre-existing increase in intracranial pressure. In patients who may be susceptible to the intracranial effects of CO2 retention (e.g., those with evidence of increased intracranial pressure or brain tumors), TUXARIN ER may reduce respiratory drive, and the resultant CO2 retention can further increase intracranial pressure. Furthermore, opioids produce adverse reactions that may obscure the clinical course of patients with head injuries.

5.12 Increased Risk of Seizures in Patients with Seizure Disorders

The codeine and chlorpheniramine in TUXARIN ER may increase the frequency of seizures in patients with seizure disorders, and may increase the risk of seizures occurring in other clinical settings associated with seizures. Monitor patients with a history of seizure disorders for worsened seizure control during TUXARIN ER therapy.

5.13 Co-administration with Monoamine Oxidase Inhibitors (MAOIs)

Concurrent use of TUXARIN ER is contraindicated in patients receiving monoamine oxidase inhibitors (MAOIs) or within 14 days of stopping such therapy [see Contraindications (4)]. MAOIs may potentiate the effects of morphine, codeine's active metabolite, including respiratory depression, coma, and confusion MAOIs [see Drug Interactions (7.7)].

5.14 Severe Hypotension

TUXARIN ER may cause severe hypotension including orthostatic hypotension and syncope in ambulatory patients. There is increased risk in patients whose ability to maintain blood pressure has already been compromised by a reduced blood volume or concurrent administration of certain CNS depressant drugs (e.g., phenothiazines or general anesthetics) [see Drug Interactions (7.5)]. Monitor these patients for signs of hypotension after initiating TUXARIN ER.

In patients with circulatory shock, TUXARIN ER may cause vasodilation that can further reduce cardiac output and blood pressure. Avoid the use of TUXARIN ER in patients with circulatory shock.

5.15 Neonatal Opioid Withdrawal Syndrome

TUXARIN ER is not recommended for use in pregnant women. Prolonged use of TUXARIN ER during pregnancy can result in withdrawal in the neonate. Neonatal opioid withdrawal syndrome, unlike opioid withdrawal syndrome in adults, may be life-threatening if not recognized and treated, and requires management according to protocols developed by neonatology experts. Observe newborns for signs of neonatal opioid withdrawal syndrome and manage accordingly. Advise pregnant women using opioids for a prolonged period of the risk of neonatal opioid withdrawal syndrome and ensure that appropriate treatment will be available. [see Use in Specific Populations (8.1), Patient Counseling Information (17)]

5.16 Adrenal Insufficiency

Cases of adrenal insufficiency have been reported with opioid use, more often following greater than one month of use. Presentation of adrenal insufficiency may include non-specific symptoms and signs including nausea, vomiting, anorexia, fatigue, weakness, dizziness, and low blood pressure. If adrenal insufficiency is suspected, confirm the diagnosis with diagnostic testing as soon as possible. If adrenal insufficiency is diagnosed, treat with physiologic replacement doses of corticosteroids. Wean the patient off of the opioid to allow adrenal function to recover and continue corticosteroid treatment until adrenal function recovers. Other opioids may be tried as some cases reported use of a different opioid without recurrence of adrenal insufficiency. The information available does not identify any particular opioids as being more likely to be associated with adrenal insufficiency.

5.17 Drug/Laboratory Test Interactions

Because opioid agonists may increase biliary tract pressure, with resultant increase in plasma amylase or lipase levels, determination of these enzyme levels may be unreliable for 24 hours after administration of a dose of TUXARIN ER.

6 ADVERSE REACTIONS

The following serious adverse reactions are described, or described in greater detail, in other sections:

- Addiction, abuse, and misuse [see Warnings and Precautions (5.1), Drug Abuse and Dependence (9.3)]
- Life-threatening respiratory depression [see Warnings and Precautions (5.2, 5.3, 5.4, 5.5, 5.9), Overdosage (10)]
- Ultra-rapid metabolism of codeine and other risk factors for life-threatening respiratory depression in children [see Warnings and Precautions (5.3)]
- Accidental overdose and death due to medication errors [see Warnings and Precautions (5.6)]
- Decreased mental alertness with impaired mental and/or physical abilities [see Warnings and Precautions (5.7)]
- Interactions with benzodiazepines and other CNS depressants [see Warnings and Precautions (5.9)]
- Paralytic ileus, gastrointestinal adverse reactions [see Warnings and Precautions (5.10)]
- Increased intracranial pressure [see Warnings and Precautions (5.11)]
- Obscured clinical course in patients with head injuries [see Warnings and Precautions (5.11)]
- Seizures [see Warnings and Precautions (5.12)]
- Interactions with MAOI [see Warnings and Precautions (5.13)]
- Severe hypotension [see Warnings and Precautions (5.14)]
- Neonatal Opioid Withdrawal Syndrome [see Warnings and Precautions (5.15)]
- Adrenal insufficiency [see Warnings and Precautions (5.16)]

The following adverse reactions have been identified during clinical studies, or during post-approval use of codeine and/or chlorpheniramine. Because these reactions may be reported voluntarily from a population of uncertain size, it is not always possible to reliably estimate their frequency or establish a causal relationship to drug exposure.

The most common adverse reactions to TUXARIN ER include: Sedation (somnolence, mental clouding, lethargy), impaired mental and physical performance, lightheadedness, dizziness, headache, dry mouth, nausea, vomiting, constipation, shortness of breath, and sweating.

Other reactions include:

Anaphylaxis: Anaphylaxis has been reported with codeine, one of the ingredients in TUXARIN ER.

Body as a whole: Coma, death, fatigue, falling injuries, lethargy.

Cardiovascular: Peripheral edema, increased blood pressure, decreased blood pressure, tachycardia, chest pain, palpitation, syncope, orthostatic hypotension, prolonged QT interval, hot flush.

Central Nervous System: Ataxia, facial dyskinesia, insomnia, increased intracranial pressure, migraine, seizure, tremor, tinnitus, vertigo.

Dermatologic: Flushing, hyperhidrosis, pruritus, rash.

Endocrine/Metabolic: Cases of serotonin syndrome, a potentially life-threatening condition, have been reported during concomitant use of opioids with serotonergic drugs. Cases of adrenal insufficiency have been reported with opioid use, more often following greater than one month of use. Cases of androgen deficiency have occurred with chronic use of opioids [see Clinical Pharmacology (12.2)].

Gastrointestinal: Abdominal pain, bowel obstruction, decreased appetite, diarrhea, difficulty swallowing, GERD, indigestion, pancreatitis, paralytic ileus, biliary tract spasm (spasm of the sphincter of Oddi).

Genitourinary: Urinary tract infection, ureteral spasm, spasm of vesicle sphincters, urinary retention.

Hematologic: Agranulocytosis, aplastic anemia, and thrombocytopenia have been reported.

Laboratory: Increases in serum amylase.

Musculoskeletal: Arthralgia, backache, muscle spasm.

Ophthalmic: Blurred vision, diplopia, miosis (constricted pupils), visual disturbances.

Psychiatric: Agitation, anxiety, confusion, fear, dysphoria, depression, hallucinations.

Reproductive: Hypogonadism, infertility.

Respiratory: Bronchitis, cough, dry nose, dry throat, dyspnea, nasal congestion, nasopharyngitis, respiratory depression, sinusitis, thickening of bronchial secretions, tightness of chest and wheezing, upper respiratory tract infection.

Other: Drug abuse, drug dependence, opioid withdrawal syndrome.

Hypoglycemia: Cases of hypoglycemia have been reported in patients taking opioids. Most reports were in patients with at least one predisposing risk factor (e.g., diabetes).

7 DRUG INTERACTIONS

No specific drug interaction studies have been conducted with TUXARIN ER.

7.1 Inhibitors of CYP3A4

The concomitant use of TUXARIN ER with CYP3A4 inhibitors, such as macrolide antibiotics (e.g., erythromycin), azole-antifungal agents (e.g. ketoconazole), or protease inhibitors (e.g., ritonavir), may result in an increase in codeine plasma concentrations with subsequently greater metabolism by cytochrome CYP2D6, resulting in greater morphine levels, which could increase or prolong adverse reactions and may cause potentially fatal respiratory depression, particularly when an inhibitor is added after a stable dose of TUXARIN ER is achieved [see Warnings and Precautions (5.8)]. After stopping a CYP3A4 inhibitor, as the effects of the inhibitor decline, it may result in lower codeine levels, greater norcodeine levels, and less metabolism via CYP2D6 with resultant lower morphine levels [see Clinical Pharmacology (12.3)], resulting in decreased opioid efficacy or a withdrawal syndrome in patients who had developed physical dependence to codeine.

Avoid the use of TUXARIN ER while taking a CYP3A4 inhibitor. If concomitant use is necessary, monitor patients for respiratory depression and sedation at frequent intervals.

7.2 CYP3A4 Inducers

The concomitant use of TUXARIN ER and CYP3A4 inducers, such as rifampin, carbamazepine, or phenytoin, can result in lower codeine levels, greater norcodeine levels, and less metabolism via 2D6 with resultant lower morphine levels [see Clinical Pharmacology (12.3)], resulting in decreased efficacy or onset of a withdrawal syndrome in patients who have developed physical dependence [see Warnings and Precautions (5.8)]. After stopping a CYP3A4 inducer, as the effects of the inducer decline, codeine plasma concentrations may increase with subsequently greater metabolism by cytochrome CYP2D6, resulting in greater morphine levels [see Clinical Pharmacology (12.3)], which could increase or prolong both the therapeutic effects and adverse reactions, and may cause serious respiratory depression.

Avoid the use of TUXARIN ER in patients who are taking CYP3A4 inducers. If concomitant use of a CYP3A4 inducer is necessary, follow the patient for reduced efficacy.

7.3 Phenytoin

Adverse event reports in the literature suggest a possible drug interaction involving increased serum phenytoin levels and phenytoin toxicity when chlorpheniramine and phenytoin are co-administered. The exact mechanism for this interaction is not known, however it is believed that chlorpheniramine may inhibit the hepatic metabolism of phenytoin. Avoid the use of TUXARIN ER while taking phenytoin.

7.4 Inhibitors of CYP2D6

Codeine is metabolized by CYP2D6 to form morphine. The concomitant use of TUXARIN ER and CYP2D6 inhibitors, such as paroxetine, fluoxetine, bupropion, or quinidine, can increase the plasma concentration of codeine, but can decrease the plasma concentration of active metabolite morphine, which could result in reduced efficacy [see Clinical Pharmacology (12.3)]. After stopping a CYP2D6 inhibitor, as the effects of the inhibitor decline, the codeine plasma concentration will decrease but the active metabolite morphine plasma concentration will increase, which could increase or prolong adverse reactions and may cause potentially fatal respiratory depression [see Clinical Pharmacology (12.3)].

Avoid the use of TUXARIN ER in patients who are taking inhibitors of CYP2D6.

7.5 Benzodiazepines and Other CNS Depressants

Due to additive pharmacologic effect, the concomitant use of benzodiazepines or other CNS depressants, including alcohol, other sedatives/hypnotics, anxiolytics, tranquilizers, muscle relaxants, general anesthetics, antipsychotics, and other opioids, can increase the risk of hypotension, respiratory depression, profound sedation, coma, and death. Avoid the use of TUXARIN ER in patients who are taking benzodiazepines or other CNS depressants. [see Warnings and Precautions (5.9)].

7.6 Serotonergic Drugs

The concomitant use of opioids with other drugs that affect the serotonergic neurotransmitter system has resulted in serotonin syndrome. If concomitant use is warranted, carefully observe the patient, particularly during treatment initiation. Discontinue TUXARIN ER if serotonin syndrome is suspected.

7.7 Monoamine Oxidase Inhibitors (MAOIs)

TUXARIN ER is contraindicated in patients who are taking MAOIs (i.e., certain drugs used for depression, psychiatric or emotional conditions, or Parkinson's disease) or have taken MAOIs within 14 days [see Contraindications (4)].

MAOI interactions with opioids may manifest as serotonin syndrome or opioid toxicity (e.g., respiratory depression, coma) [see Warnings and Precautions (5.13)].

7.8 Muscle Relaxants

Codeine may enhance the neuromuscular blocking action of skeletal muscle relaxants and produce an increased degree of respiratory depression. Avoid the use of TUXARIN ER in patients taking muscle relaxants. If concomitant use is necessary, monitor patients for signs of respiratory depression that may be greater than otherwise expected.

7.9 Diuretics

Opioids can reduce the efficacy of diuretics by inducing the release of antidiuretic hormone. Monitor patients for signs of diminished diuresis and/or effects on blood pressure and increase the dosage of the diuretic as needed.

7.10 Anticholinergic Drugs

The concomitant use of anticholinergic drugs with TUXARIN ER may increase risk of urinary retention and/or severe constipation, which may lead to paralytic ileus [see Warnings and Precautions (5.10)]. Monitor patients for signs of urinary retention or reduced gastric motility when TUXARIN ER is used concomitantly with anticholinergic drugs.

Additive adverse effects resulting from cholinergic blockade (e.g., xerostomia, blurred vision, or constipation) may occur when anticholinergic drugs are administered with chlorpheniramine.

8 USE IN SPECIFIC POPULATIONS

8.1 Pregnancy

Risk Summary

TUXARIN ER is not recommended for use in pregnant women, including during or immediately prior to labor. Prolonged use of opioids during pregnancy may cause neonatal opioid withdrawal syndrome [see Warnings and Precautions (5.15) and Clinical Considerations].

There are no available data with TUXARIN ER use in pregnant women to inform a drug-associated risk for adverse developmental outcomes. Published studies with codeine have reported inconsistent findings and have important methodological limitations (see Data). There are reports of respiratory depression when codeine is used during labor and delivery (see Clinical Considerations).

Reproductive toxicity studies have not been conducted with TUXARIN ER; however, studies are available with individual active ingredients (see Data).

In animal reproduction studies, codeine administered by the oral route to pregnant rats during the period of organogenesis increased resorptions and decreased fetal weights at a dose approximately 15 times the maximum recommended human dose (MRHD) in the presence of maternal toxicity (see Data).

Chlorpheniramine administered by the oral route to mice throughout pregnancy was embryolethal at a dose approximately 9 times the MRHD and decreased postnatal survival when dosing was continued after parturition. Chlorpheniramine administered by the oral route to male and female rats prior to mating produced embryolethality at a dose approximately 9 times the MRHD (see Data).

Based on the animal data, advise pregnant women of the potential risk to a fetus.

The estimated background risk of major birth defects and miscarriage for the indicated population is unknown. All pregnancies have a background risk of birth defect, loss, or other adverse outcomes. In the U.S. general population, the estimated background risk of major birth defects and miscarriage in clinically recognized pregnancies is 2 to 4% and 15 to 20%, respectively.

Clinical Considerations

Fetal/Neonatal Adverse Reactions

Prolonged use of opioid analgesics during pregnancy for medical or nonmedical purposes can result in physical dependence in the neonate and neonatal opioid withdrawal syndrome shortly after birth.

Neonatal opioid withdrawal syndrome presents as irritability, hyperactivity and abnormal sleep pattern, high pitched cry, tremor, vomiting, diarrhea and failure to gain weight. The onset, duration, and severity of neonatal opioid withdrawal syndrome vary based on the specific opioid used, duration of use, timing and amount of last maternal use, and rate of elimination of the drug by the newborn. Observe newborns for symptoms of neonatal opioid withdrawal syndrome and manage accordingly [see Warnings and Precautions (5.15)].

Labor or Delivery

Opioids cross the placenta and may produce respiratory depression and psycho-physiologic effects in neonates. An opioid antagonist, such as naloxone, must be available for reversal of opioid-induced respiratory depression in the neonate. Opioids, including TUXARIN ER, can prolong labor through actions which temporarily reduce the strength, duration, and frequency of uterine contractions. However, this effect is not consistent and may be offset by an increased rate of cervical dilation, which tends to shorten labor. Monitor neonates exposed to opioids during labor for signs of excess sedation and respiratory depression.

Data

Human Data

No new primary pharmacodynamic studies were conducted. Codeine is a well-established antitussive and chlorpheniramine maleate is a recognized antihistamine. Both drugs have been used at these strengths in combination for several years.

Codeine

Published data from case-control and observational studies on codeine use during pregnancy are inconsistent in their findings. Some studies of codeine exposure showed an increased risk of overall congenital malformations while others did not. An increased risk of specific malformations with codeine exposure such as respiratory malformations, spina bifida and congenital heart defects were reported in some studies. Most of the studies, both positive and negative, were limited by small sample size, recall bias and lack of information regarding dose and timing of exposure.

Chlorpheniramine

The majority of studies examining the use of chlorpheniramine in pregnancy did not find an association with an increased risk of congenital anomalies. In the few studies reporting an association, there was no consistent pattern of malformations noted.

Animal Data

Reproductive toxicity studies have not been conducted with TUXARIN ER; however, studies are available with individual active ingredients.

Codeine

In an embryofetal development study in pregnant rats dosed throughout the period of organogenesis, codeine increased resorptions and decreased fetal weights at a dose approximately 15 times the MRHD (on a mg/m^2 basis with a maternal oral dose of 120 mg/kg/day); however, these effects occurred in the presence of maternal toxicity. In embryofetal development studies with pregnant rabbits and mice dosed throughout the period of organogenesis, codeine produced no adverse developmental effects at doses approximately 7 and 35 times, respectively, the MRHD (on a mg/m^2 basis with maternal oral doses of 30 mg/kg/day in rabbits and 600 mg/kg/day in mice).

Chlorpheniramine

In embryofetal development studies with pregnant rats and rabbits dosed throughout the period of organogenesis, chlorpheniramine produced no adverse developmental effects at oral doses up to approximately 35 and 45 times, respectively, the MRHD on a mg/m^2 basis. However, in a reproduction study with pregnant mice dosed throughout pregnancy, chlorpheniramine produced embryolethality at a dose approximately 9 times the MRHD (on a mg/m^2 basis with a maternal oral dose of 20 mg/kg/day) and decreased postnatal survival when dosing was continued after parturition. In a fertility and reproduction study with male and female rats dosed prior to mating, chlorpheniramine produced embryolethality at a dose approximately 9 times the MRHD (on a mg/m^2 basis with an oral parental dose of 10 mg/kg/day).

8.2 Lactation

Risk Summary

Because of the potential for serious adverse reactions, including excess sedation, respiratory depression, and death in a breastfed infant, advise patients that breastfeeding is not recommended during treatment with TUXARIN ER [see Warnings and Precautions (5.3)].

There are no data on the presence of TUXARIN ER in human milk, the effects of TUXARIN ER on the breastfed infant, or the effects of TUXARIN ER on milk production; however, data are available with codeine and chlorpheniramine.

Codeine

Codeine and its active metabolite, morphine, are present in human milk. There are published studies and cases that have reported excessive sedation, respiratory depression and death (in one infant) in infants exposed to codeine via breast milk. Women who are ultra-rapid metabolizers of codeine achieve higher than expected serum levels of morphine, potentially leading to higher levels of morphine in breast milk that can be dangerous in their breastfed infants. In women with normal codeine metabolism (normal CYP2D6 activity), the amount of codeine secreted into human milk is low and dose-dependent. There is no information on the effects of the codeine on milk production.

Chlorpheniramine

Chlorpheniramine is present in human milk. Chlorpheniramine has not been reported to cause effects on the breastfed infant. The published literature suggests that chlorpheniramine may decrease milk production based on its anticholinergic effects. (see Clinical Considerations)

Clinical Considerations

Infants exposed to TUXARIN ER through breast milk should be monitored for excess sedation and respiratory depression. Withdrawal symptoms can occur in breastfed infants when maternal administration of an opioid is stopped, or when breastfeeding is stopped.

8.3 Females and Males of Reproductive Potential

Infertility

Chronic use of opioids, such as codeine, a component of TUXARIN ER, may cause reduced fertility in females and males of reproductive potential. It is not known whether these effects on fertility are reversible [see Adverse Reactions (6), Clinical Pharmacology (12.2)].

8.4 Pediatric Use

TUXARIN ER is not indicated for use in patients younger than 18 years of age because the benefits of symptomatic treatment of cough associated with allergies or the common cold do not outweigh the risks for use of codeine in these patients [see Indications (1), Warnings and Precautions (5.4)].

Life-threatening respiratory depression and death have occurred in children who received codeine [see Warnings and Precautions (5.2)]. In most of the reported cases, these events followed tonsillectomy and/or adenoidectomy, and many of the children had evidence of being ultra-rapid metabolizers of codeine (i.e., multiple copies of the gene for cytochrome P450 isoenzyme 2D6 or high morphine concentrations). Children with sleep apnea may be particularly sensitive to the respiratory depressant effects of codeine.

Because of the risk of life-threatening respiratory depression and death:

- TUXARIN ER is contraindicated in all children younger than 12 years of age [see Contraindications (4)].
- TUXARIN ER is contraindicated for post-operative management in pediatric patients younger than 18 years of age following tonsillectomy and/or adenoidectomy [see Contraindications (4)].
- Avoid the use of TUXARIN ER in adolescents 12 to 18 years of age who have other risk factors that may increase their sensitivity to the respiratory depressant effects of codeine unless the benefits outweigh the risks. Risk factors include conditions associated with hypoventilation, such as postoperative status, obstructive sleep apnea, obesity, severe pulmonary disease, neuromuscular disease, and concomitant use of other medications that cause respiratory depression. [see Warnings and Precautions (5.3)].

8.5 Geriatric Use

Clinical studies have not been conducted with TUXARIN ER in geriatric populations.

Use caution when considering the use of TUXARIN ER in patients 65 years of age or older. Elderly patients may have increased sensitivity to codeine; greater frequency of decreased hepatic, renal, or cardiac function; or concomitant disease or other drug therapy [see Warnings and Precautions (5.5)].

Respiratory depression is the chief risk for elderly patients treated with opioids, including TUXARIN ER. Respiratory depression has occurred after large initial doses of opioids were administered to patients who were not opioid-tolerant or when opioids were co-administered with other agents that depress respiration [see Warnings and Precautions (5.5, 5.9)].

Codeine is known to be substantially excreted by the kidney, and the risk of adverse reactions to this drug may be greater in patients with impaired renal function. Because elderly patients are more likely to have decreased renal function, monitor these patients closely for respiratory depression, sedation, and hypotension.

8.6 Renal Impairment

The pharmacokinetics of TUXARIN ER has not been characterized in patients with renal impairment. Codeine pharmacokinetics may be altered in patients with renal failure. Clearance may be decreased and the metabolites may accumulate to much higher plasma levels in patients with renal failure as compared to patients with normal renal function. Chlorpheniramine is cleared substantially by the kidney. As such, impaired renal function could potentially lead to the risk of decreased clearance and thereby increased retention or systemic levels of chlorpheniramine. Therefore, TUXARIN ER should be used with caution in patients with severe impairment of renal function, and patients should be monitored closely for signs of hydrocodone toxicity (respiratory depression, sedation, and hypotension) and chlorpheniramine toxicity.

8.7 Hepatic Impairment

No formal studies have been conducted in patients with hepatic impairment so the pharmacokinetics of TUXARIN ER in this patient population are unknown. Chlorpheniramine is extensively metabolized by liver before elimination from the body. As such, impaired hepatic function could potentially lead to the risk of decreased metabolism and thereby increased systemic levels of chlorpheniramine. Therefore, TUXARIN ER should be used with caution in patients with severe impairment of hepatic function, and patients should be monitored closely for signs of hydrocodone toxicity (respiratory depression, sedation, and hypotension) and chlorpheniramine toxicity.

9 DRUG ABUSE AND DEPENDENCE

9.1 Controlled Substance

TUXARIN ER contains codeine, a Schedule III controlled substance.

9.2 Abuse

Codeine

TUXARIN ER contains codeine, a substance with a high potential for abuse similar to other opioids including morphine and codeine. TUXARIN ER can be abused and is subject to misuse, addiction, and criminal diversion [see Warnings and Precautions (5.1)].

All patients treated with opioids require careful monitoring for signs of abuse and addiction, since use of opioid analgesic and antitussive products carries the risk of addiction even under appropriate medical use.

Prescription drug abuse is the intentional non-therapeutic use of a prescription drug, even once, for its rewarding psychological or physiological effects.

Drug addiction is a cluster of behavioral, cognitive, and physiological phenomena that develop after repeated substance use and includes: a strong desire to take the drug, difficulties in controlling its use, persisting in its use despite harmful consequences, a higher priority given to drug use than to other activities and obligations, increased tolerance, and sometimes a physical withdrawal.

"Drug-seeking" behavior is very common in persons with substance use disorders. Drug-seeking tactics include emergency calls or visits near the end of office hours, refusal to undergo appropriate examination, testing, or referral, repeated "loss" of prescriptions, tampering with prescriptions, and reluctance to provide prior medical records or contact information for other treating health care provider(s). "Doctor shopping" (visiting multiple prescribers to obtain additional prescriptions) is common among drug abusers and people suffering from untreated addiction. Preoccupation with achieving adequate pain relief can be appropriate behavior in a patient with poor pain control.

Abuse and addiction are separate and distinct from physical dependence and tolerance. Health care providers should be aware that addiction may not be accompanied by concurrent tolerance and symptoms of physical dependence in all addicts. In addition, abuse of opioids can occur in the absence of true addiction.

TUXARIN ER, like other opioids, can be diverted for non-medical use into illicit channels of distribution. Careful record-keeping of prescribing information, including quantity, frequency, and renewal requests, as required by state and federal law, is strongly advised.

Proper assessment of the patient, proper prescribing practices, periodic re-evaluation of therapy, and proper dispensing and storage are appropriate measures that help to limit abuse of opioid drugs.

Risks Specific to Abuse of TUXARIN ER

TUXARIN ER is for oral use only. Abuse of TUXARIN ER poses a risk of overdose and death. The risk is increased with concurrent use of TUXARIN ER with alcohol and other central nervous system depressants [see Warnings and Precautions (5.9)].

Parenteral drug abuse is commonly associated with transmission of infectious diseases such as hepatitis and HIV.

9.3 Dependence

Psychological dependence, physical dependence, and tolerance may develop upon repeated administration of opioids; therefore, TUXARIN ER should be prescribed and administered for the shortest duration that is consistent with individual patient treatment goals and patients should be reevaluated prior to refills [see Dosage and Administration (2.3), Warnings and Precautions (5.1)].

Physical dependence, the condition in which continued administration of the drug is required to prevent the appearance of a withdrawal syndrome, assumes clinically significant proportions only after several weeks of continued oral opioid use, although some mild degree of physical dependence may develop after a few days of opioid therapy.

If TUXARIN ER is abruptly discontinued in a physically-dependent patient, a withdrawal syndrome may occur. Withdrawal also may be precipitated through the administration of drugs with opioid antagonist activity (e.g., naloxone, nalmefene), mixed agonist/antagonist analgesics (e.g., pentazocine, butorphanol, nalbuphine), or partial agonists (e.g., buprenorphine). Some or all of the following can characterize this syndrome: restlessness, lacrimation, rhinorrhea, yawning, perspiration, chills, myalgia, and mydriasis. Other signs and symptoms also may develop, including irritability, anxiety, backache, joint pain, weakness, abdominal cramps, insomnia, nausea, anorexia, vomiting, diarrhea, or increased blood pressure, respiratory rate, or heart rate.

Infants born to mothers physically dependent on opioids will also be physically dependent and may exhibit respiratory difficulties and withdrawal signs [see Use in Specific Populations (8.1)].

10 OVERDOSAGE

Clinical Presentation

Codeine

Acute overdose with codeine is characterized by respiratory depression (a decrease in respiratory rate and/or tidal volume, Cheyne-Stokes respiration, cyanosis), extreme somnolence progressing to stupor or coma, skeletal muscle flaccidity, cold and clammy skin, constricted pupils, and, in some cases, pulmonary edema, bradycardia, partial or complete airway obstruction, atypical snoring, hypotension, hypoglycemia, circulatory collapse, cardiac arrest, and death.

Codeine may cause miosis, even in total darkness. Pinpoint pupils are a sign of opioid overdose but are not pathognomonic (e.g., pontine lesions of hemorrhagic or ischemic origin may produce similar findings). Marked mydriasis rather than miosis may be seen with hypoxia in overdose situations [see Clinical Pharmacology (12.2)].

Chlorpheniramine

Signs and symptoms of chlorpheniramine overdosage may vary from central nervous system depression to stimulation. Central toxic effects are characterized by agitation, anxiety, delirium, disorientation, hallucinations, hyperactivity, sedation, and seizures. Severe overdosage may produce coma, medullary paralysis, and death. Peripheral toxicity includes hypertension, tachycardia, dysrhythmias, vasodilation, hyperpyrexia, mydriasis, urinary retention, and diminished gastrointestinal motility. Atropine-like signs and symptoms (dry mouth, fixed dilated pupils, flushing, tachycardia, hallucinations, gastrointestinal symptoms, convulsions, urinary retention, cardiac arrhythmias and coma) may be observed.

Impaired secretion from sweat glands following toxic doses of drugs with anticholinergic side effects may predispose to hyperthermia.

Toxic psychosis, a possible class effect from overdose of sedating antihistamines, has been reported.

Treatment of Overdose

Treatment of overdosage is driven by the overall clinical presentation, and consists of discontinuation of TUXARIN ER together with institution of appropriate therapy. Give primary attention to the reestablishment of adequate respiratory exchange through provision of a patent and protected airway and the institution of assisted or controlled ventilation. Employ other supportive measures (including oxygen and vasopressors) in the management of circulatory shock and pulmonary edema as indicated. Cardiac arrest or arrhythmias will require advanced life-support techniques. Gastric emptying may be useful in removing unabsorbed drug.

The opioid antagonists, naloxone and nalmefene, are specific antidotes for respiratory depression resulting from opioid overdose. For clinically significant respiratory or circulatory depression secondary to codeine overdose, administer an opioid antagonist. An antagonist should not be administered in the absence of clinically significant respiratory depression. Because the duration of opioid reversal is expected to be less than the duration of action of codeine in TUXARIN ER, carefully monitor the patient until spontaneous respiration is reliably reestablished. TUXARIN ER will continue to release codeine and add to the codeine load for 4 hours or longer following ingestion, necessitating prolonged monitoring. If the response to an opioid antagonist is suboptimal or only brief in nature, administer additional antagonist as directed by the product's prescribing information.

Hemodialysis is not routinely used to enhance the elimination of codeine or chlorpheniramine from the body.

Urinary excretion of chlorpheniramine is increased when the pH of the urine is acidic; however, acid diuresis is NOT recommended to enhance elimination in overdose, as the risks of acidemia and acute tubular necrosis in patients with rhabdomyolysis far outweigh any potential benefits.

11 DESCRIPTION

TUXARIN ER (codeine phosphate and chlorpheniramine maleate) extended-release tablets, contains codeine, an opioid agonist; and chlorpheniramine, a histamine-1 (H1) receptor antagonist.

Each tablet of TUXARIN ER contains 54.3 mg of codeine phosphate and 8 mg of chlorpheniramine maleate for oral administration.

TUXARIN ER are white to off-white, uncoated, standard round extended-release matrix tablets.

TUXARIN ER also contains the following inactive ingredients: hypromellose, lactose monohydrate, cellulose microcrystalline, polysorbate 80, magnesium stearate, and colloidal silicon dioxide.

Codeine Phosphate

The chemical name for codeine phosphate is [morphine3methyl ether phosphate (1:1) (salt)] hemihydrate. It has the following structural formula:

Chlorpheniramine Maleate

The chemical name for chlorpheniramine maleate is 2-pyridinepropanamine, γ-(4-chlorophenyl)-N,N-dimethyl-, (Z)-2-butenedioate (1:1). It has the following structural formula:

12 CLINICAL PHARMACOLOGY

12.1 Mechanism of Action

Codeine

Codeine is an opioid agonist relatively selective for the mu-opioid receptor, but with a much weaker affinity than morphine. The analgesic and antitussive properties of codeine have been speculated to come from its conversion to morphine. The precise mechanism of action of codeine and other opiates is not known; however, codeine is believed to act centrally on the cough center. In excessive doses, codeine will depress respiration.

Chlorpheniramine

Chlorpheniramine is a propylamine derivative antihistamine (H1-receptor antagonist) of the alkylamine class that also possesses anticholinergic and sedative activity. It prevents released histamine from dilating capillaries and causing edema of the respiratory mucosa.

12.2 Pharmacodynamics

Codeine

Effects on the Central Nervous System

Codeine produces respiratory depression by direct action on brain stem respiratory centers. The respiratory depression involves a reduction in the responsiveness of the brain stem respiratory centers to both increases in carbon dioxide tension and to electrical stimulation.

Codeine causes miosis, even in total darkness. Pinpoint pupils are a sign of opioid overdose but are not pathognomonic (e.g., pontine lesions of hemorrhagic or ischemic origins may produce similar findings). Marked mydriasis rather than miosis may be seen due to hypoxia in overdose situations.

Effects on the Gastrointestinal Tract and Other Smooth Muscle

Codeine causes a reduction in motility associated with an increase in smooth muscle tone in the antrum of the stomach and duodenum. Digestion of food in the small intestine is delayed and propulsive contractions are decreased. Propulsive peristaltic waves in the colon are decreased, while tone may be increased to the point of spasm resulting in constipation. Other opioid-induced effects may include a reduction in biliary and pancreatic secretions, spasm of sphincter of Oddi, and transient elevations in serum amylase.

Effects on the Cardiovascular System

Codeine produces peripheral vasodilation which may result in orthostatic hypotension or syncope. Manifestations of histamine release and/or peripheral vasodilation may include pruritus, flushing, red eyes and sweating and/or orthostatic hypotension.

Effects on the Endocrine System

Opioids inhibit the secretion of adrenocorticotropic hormone (ACTH), cortisol, and luteinizing hormone (LH) in humans [see Adverse Reactions (6)]. They also stimulate prolactin, growth hormone (GH) secretion, and pancreatic secretion of insulin and glucagon.

Chronic use of opioids may influence the hypothalamic-pituitary-gonadal axis, leading to androgen deficiency that may manifest as low libido, impotence, erectile dysfunction, amenorrhea, or infertility. The causal role of opioids in the clinical syndrome of hypogonadism is unknown because the various medical, physical, lifestyle, and psychological stressors that may influence gonadal hormone levels have not been adequately controlled for in studies conducted to date [see Adverse Reactions (6)].

Effects on the Immune System

Opioids have been shown to have a variety of effects on components of the immune system in in vitro and animal models. The clinical significance of these findings is unknown. Overall, the effects of opioids appear to be modestly immunosuppressive.

Concentration–Adverse Reaction Relationships

There is a relationship between increasing codeine plasma concentration and increasing frequency of dose-related opioid adverse reactions such as nausea, vomiting, CNS effects, and respiratory depression. In opioid-tolerant patients, the situation may be altered by the development of tolerance to opioid-related adverse reactions.

12.3 Pharmacokinetics

Absorption

Pharmacokinetic (PK) parameters (Mean ± SD) for TUXARIN ER in fasting, healthy volunteers are shown in the table below.

PK Parameter | Single-dose |  | Multiple-dose (BID for 6.5 days)
 | Codeine Mean (± SD) | Chlorpheniramine Maleate Mean (± SD) | Codeine Mean (± SD) | Chlorpheniramine Maleate Mean (± SD)
Tmax (h) (Range) | 3 (2-12) | 6 (4-12) | 3 (2-5) | 5 (3-7)
Cmax (ng/mL) | 46 (11) | 9 (3)
AUCinf (ng.h/mL) for single-dose OR AUC12 (ng.h/mL) for multiple-dose | 383 (99) | 312 (137)
Half life (h) | 4 (1) | 21 (7) | Not determined | Not determined

Food Effect

The presence of a high-fat, high-calorie meal did not significantly impact the PK parameters of TUXARIN ER.

Distribution

Codeine has been reported to have an apparent volume of distribution of approximately 3 to 6 L/kg, indicating extensive distribution of the drug into tissues. Codeine has low plasma protein binding with about 7 to 25% of codeine bound to plasma proteins. Codeine passes the blood brain barrier and the placental barrier. Small amounts of codeine and its metabolite, morphine, are transferred to human breast milk.

Chlorpheniramine is widely distributed throughout the tissues of the body, including the central nervous system. It reportedly has an apparent steady-state volume of distribution of approximately 3.2 L/kg in adults and children and is about 70% bound to plasma proteins. Chlorpheniramine and its metabolites likely cross the placental barrier and are excreted into human breast milk.

Elimination

Metabolism

Codeine is metabolized by conjugation with glucuronic acid to codeine-6-glucuronide (about 70 to 80%), by O-demethylation to morphine (about 5 to 10%), and by N-demethylation to norcodeine (about 10%). UDP-glucuronosyltransferase (UGT) 2B7 and 2B4 are the major enzymes mediating glucuronidation of codeine to C6G. Cytochrome P450 2D6 is the major enzyme responsible for conversion of codeine to morphine and P450 3A4 is the major enzyme mediating conversion of codeine to norcodeine. Morphine and norcodeine are further metabolized by conjugation with glucuronic acid. The glucuronide metabolites of morphine are morphine-3- glucuronide (M3G) and morphine-6-glucuronide (M6G). Morphine and its M6 glucuronide conjugate are pharmacologically active. Whether C6G has pharmacological activity is unknown. Norcodeine and M3 glucuronide conjugate of morphine are generally not considered to be pharmacologically active.

Chlorpheniramine is rapidly and extensively metabolized via demethylation in the liver, forming mono-and didesmethyl derivatives. Oxidative metabolism of chlorpheniramine is catalyzed by cytochrome P-450 2D6.

Excretion

Approximately 90% of the total dose of codeine is excreted through the kidneys, of which approximately 10% is unchanged codeine. The mean plasma half-life of codeine was about 4 hours with TUXARIN ER.

Chlorpheniramine and its metabolites are primarily excreted through the kidneys, with large individual variation. Urinary excretion depends on urine pH and flow rate. The mean plasma half-life of chlorpheniramine was approximately 21 hours with TUXARIN ER.

13 NONCLINICAL TOXICOLOGY

13.1 Carcinogenesis, Mutagenesis, Impairment of Fertility

Carcinogenicity, mutagenicity, and fertility studies have not been conducted with TUXARIN ER; however, published information is available for the active ingredients.

Codeine

Carcinogenicity studies were conducted with codeine. Two-year studies in F344/N rats and B6C3F1 mice were conducted to assess the carcinogenic potential of codeine. No evidence of tumorigenicity was observed in male and female rats at codeine dietary doses up to 70 and 80 mg/kg/day (approximately equivalent to 9 and 10 times, the MRHD on a mg/m^2 basis, respectively). No evidence of tumorigenicity was observed in male and female mice at codeine dietary doses up to 400 mg/kg/day (approximately equivalent to 25 times the MRHD on a mg/m^2 basis).

Codeine was not mutagenic in the in vitro bacterial reverse mutation assay or clastogenic in the in vitro Chinese hamster ovary (CHO) cell chromosomal aberration assay.

Fertility studies with codeine have not been conducted.

Chlorpheniramine

Carcinogenicity studies were conducted with chlorpheniramine maleate. Two-year studies in F344/N rats and B6C3F1 mice were conducted to assess the carcinogenic potential of chlorpheniramine. No evidence of tumorigenicity was observed in male and female rats at chlorpheniramine oral doses up to 30 and 60 mg/kg/day for 5 days/week (approximately equivalent to 25 and 50 times the MRHD on a mg/m^2 basis, respectively). No evidence of tumorigenicity was observed in male and female mice at chlorpheniramine oral doses up to 50 and 200 mg/kg/day for 5 days/week (approximately equivalent to 20 and 85 times the MRHD on a mg/m^2 basis, respectively).

Chlorpheniramine maleate was not mutagenic in the in vitro bacterial reverse mutation assay or the in vitro mouse lymphoma forward mutation assay. Chlorpheniramine maleate was clastogenic in the in vitro Chinese hamster ovary (CHO) cell chromosomal aberration assay.

Chlorpheniramine maleate had no effects on fertility in rats and rabbits at oral doses approximately 35 and 45 times the MRHD on a mg/m^2 basis, respectively.

16 HOW SUPPLIED/STORAGE AND HANDLING

TUXARIN ER (codeine phosphate and chlorpheniramine maleate) 54.3 mg/ 8 mg extended-release tablets, are white to off-white, uncoated, standard round tablets, debossed with MP on one side and CC on the other side. Supplied in bottles of 30 tablets (NDC 71269-040-30) and 100 tablets (NDC 71269-040-10).

STORAGE AND HANDLING

Store at 20 to 25°C (68 to 77°F) [see USP Controlled Room Temperature].

Dispense in a tight, light-resistant container, as defined in the USP, with a child-resistant closure.

Keep this and all medicine out of reach of children.

17 PATIENT COUNSELING INFORMATION

Advise the patient to read the FDA-approved patient labeling (Medication Guide).

Addiction, Abuse, and Misuse

Inform patients that the use of TUXARIN ER, even when taken as recommended, can result in addiction, abuse, and misuse, which can lead to overdose and death [see Warnings and Precautions (5.1)]. Instruct patients not to share TUXARIN ER with others and to take steps to protect TUXARIN ER from theft or misuse.

Important Dosing and Administration Instructions

Advise patients take TUXARIN ER exactly as prescribed. Advise patients not to increase the dose or dosing frequency of TUXARIN ER because serious adverse events such as respiratory depression may occur with overdosage [see Warnings and Precautions (5.2), Overdosage (10)].

Life-Threatening Respiratory Depression

Inform patients of the risk of life-threatening respiratory depression, including information that the risk is greatest when starting TUXARIN ER and that it can occur even at recommended dosages [see Warnings and Precautions (5.2)]. Advise patients how to recognize respiratory depression and to seek medical attention if breathing difficulties develop.

Accidental Ingestion

Inform patients that accidental ingestion, especially by children, may result in respiratory depression or death [see Warnings and Precautions (5.2)]. Instruct patients to take steps to store TUXARIN ER securely and to properly dispose of unused TUXARIN ER in accordance with the local state guidelines and/or regulations.

Ultra-Rapid Metabolism of Codeine and Other Risk Factors for Life-Threatening Respiratory Depression in Children

Advise caregivers that TUXARIN ER is not indicated for pediatric patients under 18 years of age and is contraindicated in all children younger than 12 years of age and in children younger than 18 years of age following tonsillectomy and/or adenoidectomy.

Activities Requiring Mental Alertness

Advise patients to avoid engaging in hazardous tasks that require mental alertness and motor coordination such as operating machinery or driving a motor vehicle as TUXARIN ER may produce marked drowsiness [see Warnings and Precautions (5.7)].

Interactions with Benzodiazepines and Other Central Nervous System Depressants, Including Alcohol

Inform patients and caregivers that potentially fatal additive effects may occur if TUXARIN ER is used with benzodiazepines or other CNS depressants, including alcohol. Advise patients to avoid concomitant use of TUXARIN ER with benzodiazepines or other CNS depressants and to not use alcohol while taking TUXARIN ER [see Warnings and Precautions (5.9), Drug Interactions (7.5)].

Constipation

Advise patients of the potential for severe constipation [see Warnings and Precautions (5.10), Adverse Reactions (6)].

Anaphylaxis

Inform patients that anaphylaxis has been reported with ingredients contained in TUXARIN ER. Advise patients how to recognize such a reaction and when to seek medical attention [see Contraindications (4), Adverse Reactions (6)].

MAOI Interaction

Inform patients not to take TUXARIN ER while using or within 14 days of stopping any drugs that inhibit monoamine oxidase. Patients should not start MAOIs while taking TUXARIN ER [see Warnings and Precautions (5.13), Drug Interactions (7.7)].

Hypotension

Inform patients that TUXARIN ER may cause orthostatic hypotension and syncope. Instruct patients how to recognize symptoms of low blood pressure and how to reduce the risk of serious consequences should hypotension occur (e.g., sit or lie down, carefully rise from a sitting or lying position) [see Warnings and Precautions (5.14)].

Pregnancy

Advise patients that use of TUXARIN ER is not recommended during pregnancy [see Use in Specific Populations (8.1)].

Neonatal Opioid Withdrawal Syndrome

Inform female patients of reproductive potential that use of TUXARIN ER during pregnancy can result in neonatal opioid withdrawal syndrome, which may be life-threatening if not recognized and treated [see Warnings and Precautions (5.15), Use in Specific Populations (8.1)].

Embryo-Fetal Toxicity

Inform female patients of reproductive potential that TUXARIN ER can cause fetal harm and to inform their healthcare provider of a known or suspected pregnancy [see Use in Specific Populations (8.1)].

Lactation

Advise women that breastfeeding is not recommended during treatment with TUXARIN ER [see Use in Specific Populations (8.2)].

Infertility

Inform patients that chronic use of opioids, such as codeine, a component of TUXARIN ER, may cause reduced fertility. It is not known whether these effects on fertility are reversible [see Use in Specific Populations (8.3)].

Adrenal Insufficiency

Inform patients that TUXARIN ER could cause adrenal insufficiency, a potentially life-threatening condition. Adrenal insufficiency may present with non-specific symptoms and signs such as nausea, vomiting, anorexia, fatigue, weakness, dizziness, and low blood pressure. Advise patients to seek medical attention if they experience a constellation of these symptoms [see Warnings and Precautions (5.16)].

Serotonin Syndrome

Inform patients that TUXARIN ER could cause a rare but potentially life-threatening condition resulting from concomitant administration of serotonergic drugs. Warn patients of the symptoms of serotonin syndrome and to seek medical attention right away if symptoms develop. Instruct patients to inform their physicians if they are taking, or plan to take serotonergic medications. [see Adverse Reactions (6), Drug Interactions (7.6)].

Disposal of Unused TUXARIN ER

Advise patients to properly dispose of unused TUXARIN ER. Advise patients to throw the drug in the household trash following these steps. 1) Remove them from their original containers and mix them with an undesirable substance, such as used coffee grounds or kitty litter (this makes the drug less appealing to children and pets, and unrecognizable to people who may intentionally go through the trash seeking drugs). 2) Place the mixture in a sealable bag, empty can, or other container to prevent the drug from leaking or breaking out of a garbage bag, or to dispose of in accordance with local state guidelines and/or regulations.

Distributed By:
MainPointe Pharmaceuticals, LLC
Louisville, KY, 40206

7184-0000-99-OS
Rev 12/2023

Medication Guide
TUXARIN® ER (Tuks-a-ren)
(codeine phosphate and chlorpheniramine maleate)
extended-release tablets, C-III

What is the most important information I should know about TUXARIN ER?

TUXARIN ER is not for children under 18 years of age.
TUXARIN ER can cause serious side effects, including:

- Addiction, abuse and misuse. Taking TUXARIN ER or other medications that contain an opioid can cause addiction, abuse, and misuse, which can lead to overdose and death. This can happen even if you take TUXARIN ER exactly as prescribed by your healthcare provider. Your risk of addiction, abuse, and misuse is increased if you or a family member has a history of drug or alcohol abuse or addiction, or mental health problems.
  - Do not share your TUXARIN ER with other people.
  - Keep TUXARIN ER in a safe place away from children.
- Life-threatening breathing problems (respiratory depression). TUXARIN ER can cause breathing problems (respiratory depression) that can happen at any time during treatment and can lead to death. Your risk of breathing problems is greatest when you first start taking TUXARIN ER, are taking other medicines that can cause breathing problems, have certain lung problems, are elderly or have certain other health problems. Children are at higher risk for respiratory depression. Breathing problems can happen even if you take TUXARIN ER exactly as prescribed by your healthcare provider.
  Call your healthcare provider or get emergency medical help right away if anyone taking TUXARIN ER has any of the symptoms below:

- increased sleepiness
- confusion
- difficulty breathing

- shallow breathing
- limpness

Keep TUXARIN ER in a safe place away from children. Accidental use of even 1 dose of TUXARIN ER, especially by a child, is a medical emergency and can cause breathing problems (respiratory depression) which can lead to death. If a child accidentally takes TUXARIN ER, get emergency help right away.

- Overdose and death due to medicine dosing errors. Overdose and death can happen if you take the wrong dose of TUXARIN ER. Do not increase the dose or dosing frequency of TUXARIN ER. See "How should I take TUXARIN ER?"
- Breathing problems (respiratory depression) that can lead to death and opioid withdrawal can happen if you start taking or stop taking other medicines while taking TUXARIN ER, including:
  - certain antibiotics
  - certain medicines to treat a fungal infection
  - certain medicines to treat Human Immunodeficiency Virus (HIV)-1 infection, Acquired Immune Deficiency Syndrome (AIDS), or Hepatitis C
  - rifampin
  - carbamazepine
  - phenytoin
- Severe drowsiness, breathing problems (respiratory depression), coma, and death can happen in adults and children who take TUXARIN ER with benzodiazepines, or other central nervous system depressants, including alcohol.
  - Do not take any benzodiazepines or medicines that can cause drowsiness or sleepiness during treatment with TUXARIN ER. Ask your healthcare provider for a list of these medicines if you are not sure.
  - Do not drink alcohol during treatment with TUXARIN ER.
- Opioid withdrawal in a newborn. Use of TUXARIN ER during pregnancy can cause withdrawal symptoms in your newborn baby that could be life-threatening if not recognized and treated. You should not take TUXARIN ER if you are pregnant. Tell your healthcare provider right away if you are pregnant or think you may be pregnant.

What is TUXARIN ER?

- TUXARIN ER is a prescription medicine used to treat cough and upper respiratory symptoms that you can have with allergies or a common cold. TUXARIN ER contains 2 medicines, codeine and chlorpheniramine. Codeine is an opioid (narcotic) cough suppressant. Chlorpheniramine is an antihistamine.
- TUXARIN ER is a federal controlled substance (C-III) because it contains codeine that can be abused or lead to dependence. Keep TUXARIN ER in a safe place to prevent misuse and abuse. Selling or giving away TUXARIN ER may harm others and is against the law. Tell your healthcare provider if you have abused or been dependent on alcohol, prescription medicines or street drugs.

Who should not take TUXARIN ER?

TUXARIN ER is not for children under 18 years of age. See "What is the most important information I should know about TUXARIN ER?"
Do not take TUXARIN ER if you:

- have severe breathing problems (respiratory depression). See "What is the most important information I should know about TUXARIN ER?"
- have a blockage (obstruction) in your bowel such as a paralytic ileus.
- take a medicine for depression called a Monoamine Oxidase Inhibitor (MAOI).
  - Do not take an MAOI within 14 days after you stop taking TUXARIN ER.
  - Do not start taking TUXARIN ER if you stopped taking an MAOI in the last 14 days.
- are allergic to codeine, chlorpheniramine, or any of the ingredients in TUXARIN ER. See the end of this Medication Guide for a complete list of ingredients in TUXARIN ER. You may have an increased risk of having an allergic reaction to TUXARIN ER if you are allergic to certain other opioid medicines.

Ask your healthcare provider if you have any questions about this information.

Before taking TUXARIN ER, tell your healthcare provider about all of your medical conditions, including if you:

- have a drug addiction
- have lung or breathing problems
- have a fever and are coughing up mucus
- have had a recent head injury
- have had a brain tumor or other brain problems
- have or have had seizures
- have pain in your stomach-area (abdomen)
- have constipation or other bowel problems

- have bile duct or pancreas problems
- have prostate problems
- have problems with your urinary tract or difficulty urinating
- have kidney or liver problems
- have adrenal gland problems
- have low blood pressure (hypotension)
- plan to have surgery

- are pregnant or plan to become pregnant. TUXARIN ER can harm your unborn baby. See "What is the most important information I should know about TUXARIN ER?"
- are breastfeeding or plan to breastfeed. Codeine and chlorpheniramine pass into your breast milk and can cause serious side effects in your baby including increased sleepiness, breathing problems (respiratory depression) and death. You and your healthcare provider should decide if you will take TUXARIN ER or breastfeed. You should not do both. See "What should I avoid while taking TUXARIN ER?"
- plan to have children. TUXARIN ER may affect the ability to have a child in females and males (fertility problems). It is not known if these fertility problems will be reversible, even after you stop taking TUXARIN ER.

Tell your healthcare provider about all of the medicines you take, including prescription and over-the-counter medicines, vitamins, and herbal supplements.
Taking TUXARIN ER with certain other medicines can cause side effects or affect how well TUXARIN ER or the other medicines work. Do not start or stop taking other medicines without talking to your healthcare provider.
Especially tell your healthcare provider if you:

- See "What is the most important information I should know about TUXARIN ER?"
- take pain medicines such as opioids (narcotics).
- take cold or allergy medicines that contain antihistamines or cough suppressants.
- drink alcohol.
- take muscle relaxants.
- take certain medicines used to treat mood, anxiety, psychotic or thought disorders, or depression, including monoamine oxidase inhibitors (MAOIs), tricyclics, selective serotonin reuptake inhibitors (SSRIs), selective serotonin-norepinephrine reuptake inhibitors (SNRIs), or antipsychotics.
- take medicines to lower your blood pressure.
- water pills (diuretics).
- take medicines called "anticholinergics" used to treat health problems such as asthma, chronic obstructive pulmonary disease (COPD), or stomach problems.
- take a medicine called "phenytoin" used to treat seizures or epilepsy.

Ask your healthcare provider if you are not sure if you take one of these medicines.

How should I take TUXARIN ER?

- See "What is the most important information I should know about TUXARIN ER?"
- Take TUXARIN ER exactly as your healthcare provider tells you to take it. Do not change your dose without talking to your healthcare provider.
- Take TUXARIN ER by mouth only. TUXARIN ER is usually taken every 12 hours. Do not take more than 2 TUXARIN ER tablets in 24 hours.
- If you take too much TUXARIN ER, call your healthcare provider or go to the nearest hospital emergency room right away.
- Tell your healthcare provider if your cough does not get better within 5 days of treatment with TUXARIN ER.

What should I avoid doing while taking TUXARIN ER?

- Avoid driving a car or operating machinery during treatment with TUXARIN ER. TUXARIN ER can cause you to be drowsy, slow your thinking and motor skills, and affect your vision.
- Do not drink alcohol during treatment with TUXARIN ER. Drinking alcohol with TUXARIN ER can increase your chances of having serious side effects.

Avoid the use of TUXARIN ER if you:

- are pregnant. Use of TUXARIN ER during pregnancy can cause withdrawal symptoms in your newborn baby that could be life-threatening if not recognized and treated. Tell your healthcare provider right away if you are pregnant or think you may be pregnant.
- are breastfeeding. Use of TUXARIN ER while breastfeeding can cause severe breathing problems (respiratory depression) in your breastfed infant that could be life-threatening.

What are the possible side effects of TUXARIN ER?
TUXARIN ER can cause serious side effects, including:

- See "What is the most important information I should know about TUXARIN ER?"
- Bowel problems including severe constipation or stomach pain. See, "Who should not take TUXARIN ER?"
- Increased pressure in your head (intracranial). Avoid the use of TUXARIN ER if you have a head injury or have been told that you have changes in the tissue of your brain (brain lesions) or increased pressure in your head.
- Increased risk of seizures in people with seizure disorders. If you have a seizure disorder, TUXARIN ER may increase how often you have seizures.
- Low blood pressure. A sudden drop in blood pressure can happen in some people during treatment with TUXARIN ER and this may cause you to feel dizzy, faint, lightheaded, or weak, especially when you stand up (orthostatic hypotension). Your risk of having this problem may be increased if you take TUXARIN ER with certain other medicines that lower blood pressure. If you have any of these symptoms while taking TUXARIN ER, sit or lie down. Do not change your body position too fast. Get up slowly from sitting or lying down.
- Adrenal gland problems. TUXARIN ER can cause serious and life-threatening adrenal gland problems. Your healthcare provider may do blood tests to check for adrenal gland problems. Call your healthcare provider right away if you have any of these symptoms:

- nausea
- vomiting
- not wanting to eat (anorexia)
- fatigue

- weakness
- dizziness
- low blood pressure

The most common side effects of TUXARIN ER include:

- sleepiness
- confusion
- coordination problems
- decrease in mental and physical performance
- lack of energy
- lightheadedness
- dizziness

- headache
- dry mouth
- sweating
- nausea
- vomiting
- constipation

These are not all the possible side effects of TUXARIN ER.
Call your doctor for medical advice about side effects. You may report side effects to FDA at 1-800-FDA-1088.

How should I store TUXARIN ER?

- Store TUXARIN ER at room temperature between 68°F to 77°F (20°C to 25°C).
- Keep TUXARIN ER in a tightly closed container, in a dry, cool place away from heat or direct sunlight.
- Keep TUXARIN ER and all medicines out of the reach of children.

How should I dispose of TUXARIN ER?
Remove unused TUXARIN ER from the container and mix it with an undesirable, non-toxic substance such as cat litter or used coffee grounds to make it less appealing to children and pets. Place the mixture in a container such as a sealed plastic bag and throw it away in the household trash. You can also follow your state or local guidelines on how to safely throw away TUXARIN ER.

General information about the safe and effective use of TUXARIN ER.
Medicines are sometimes prescribed for purposes other than those listed in a Medication Guide. Do not use TUXARIN ER for a condition for which it was not prescribed. Do not give TUXARIN ER to other people, even if they have the same symptoms that you have. It may harm them.
You can ask your pharmacist or healthcare provider for information about TUXARIN ER that is written for health professionals.

What are the ingredients in TUXARIN ER?
Active ingredients: codeine phosphate and chlorpheniramine maleate
Inactive ingredients: Hypromellose, lactose monohydrate, cellulose microcrystalline, polysorbate 80, magnesium stearate, and colloidal silicon dioxide.
Distributed By: MainPointe Pharmaceuticals, LLC
Louisville, KY, 40206
For more information go to mainpointepharmaceuticals.com or call 502-709-7544

This Medication Guide has been approved by the U.S. Food and Drug Administration

Revised: June 2018

PRINCIPAL DISPLAY PANEL - 100 Tablet Bottle Label

NDC 71269-040-10

CIII

Tuxarin ER™
(codeine phosphate and
chlorpheniramine maleate
extended-release tablets)
54.3 mg/ 8 mg

Each Tablet Contains:
Codeine Phosphate, USP 54.3 mg
(Equivalent to 40 mg of Codeine)
Chlorpheniramine Maleate, USP 8 mg
(Equivalent to 5.6 mg of Chlorpheniramine)

PHARMACIST: PLEASE DISPENSE WITH
MEDICATION GUIDE

Rx only
100 Tablets